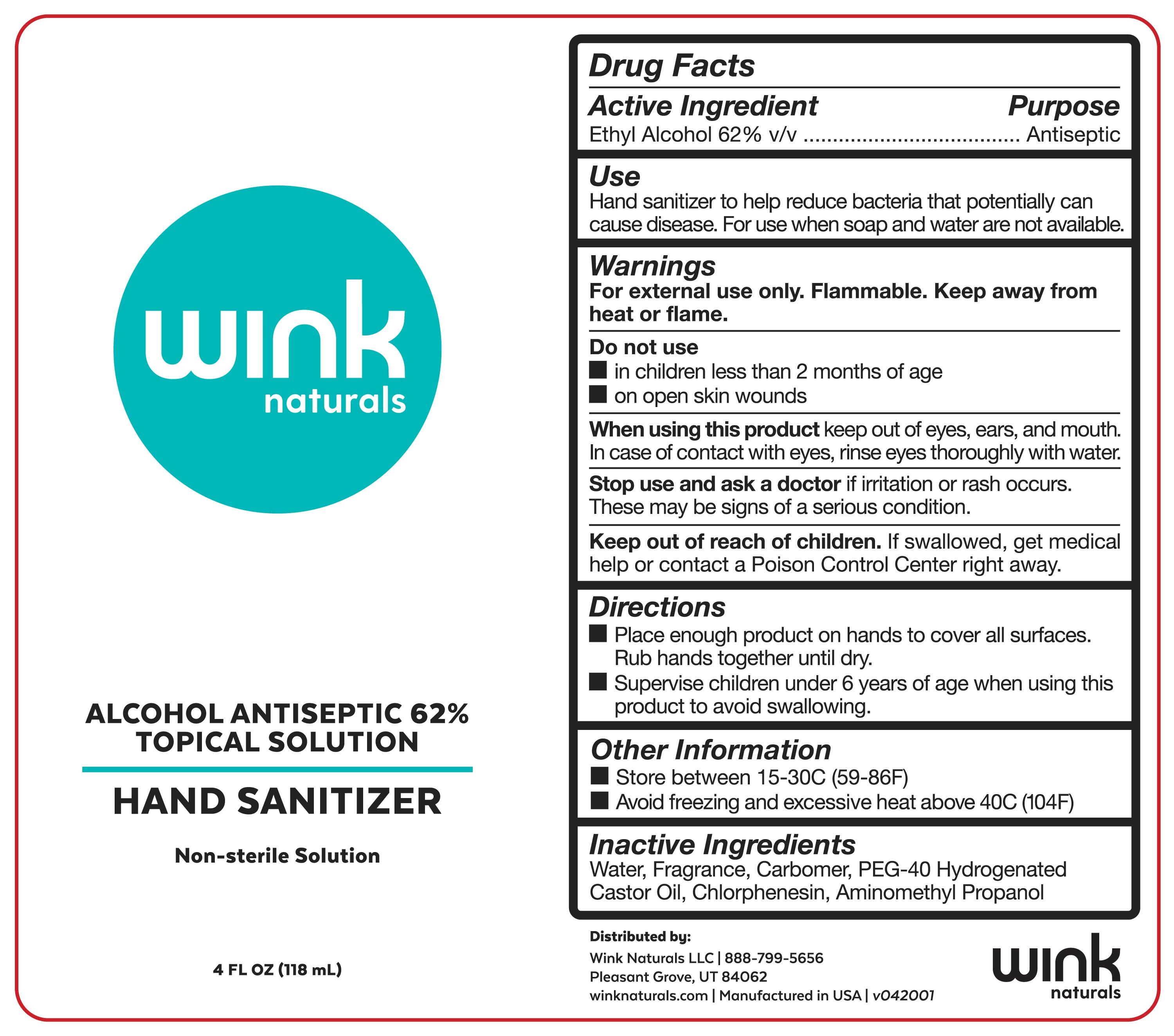 DRUG LABEL: Alcohol Antispetic 62% Topical Solution Hand Sanitizer
NDC: 77041-002 | Form: SOLUTION
Manufacturer: Wink Naturals, LLC
Category: otc | Type: HUMAN OTC DRUG LABEL
Date: 20200526

ACTIVE INGREDIENTS: ALCOHOL 62 mL/100 mL
INACTIVE INGREDIENTS: CARBOMER HOMOPOLYMER, UNSPECIFIED TYPE; POLYOXYL 40 HYDROGENATED CASTOR OIL; WATER; CHLORPHENESIN; AMINOMETHYLPROPANOL

Alcohol Antispetic 62% Topical Solution Hand Sanitizer

Active Ingredient Purpose

Alcohol 62% v/v. Antiseptic

Purpose

Antiseptic

Keep out of reach of children. If swallowed, get medical help or contact a Poison Control Center right away.

Use

Hand Sanitizer to help reduce bacteria that potentially can cause disease. For use when soap and water are not available.

Warnings

For external use only. Flammable. Keep away from heat or flame

When using this product keep out of eyes, ears, and mouth. In case of contact with eyes, rinse eyes thoroughly with water.

Stop use and ask a doctor if irritation or rash occurs. These may be signs of a serious condition.

Keep out of reach of children. If swallowed, get medical help or contact a Poison Control Center right away.

Do not use

- in children less than 2 months of age
- on open skin wounds

Directions

- Place enough product on hands to cover all surfaces. Rub hands together until dry.
- Supervise children under 6 years of age when using this product to avoid swallowing.

Other information

- Store between 15-30C (59-86F)
- Avoid freezing and excessive heat above 40C (104F)

Inactive ingredients

Water, Fragrance, Carbomer, PEG-40 Hydrogenated Castor Oil, Chlorphenesin, Aminomethyl Propanol

Package Label - Principal Display Panel

Wink Naturals

Alcohol Antiseptic 62% Topical Solution

Hand Sanitizer

Non-sterile

4 FL OZ (118 mL)